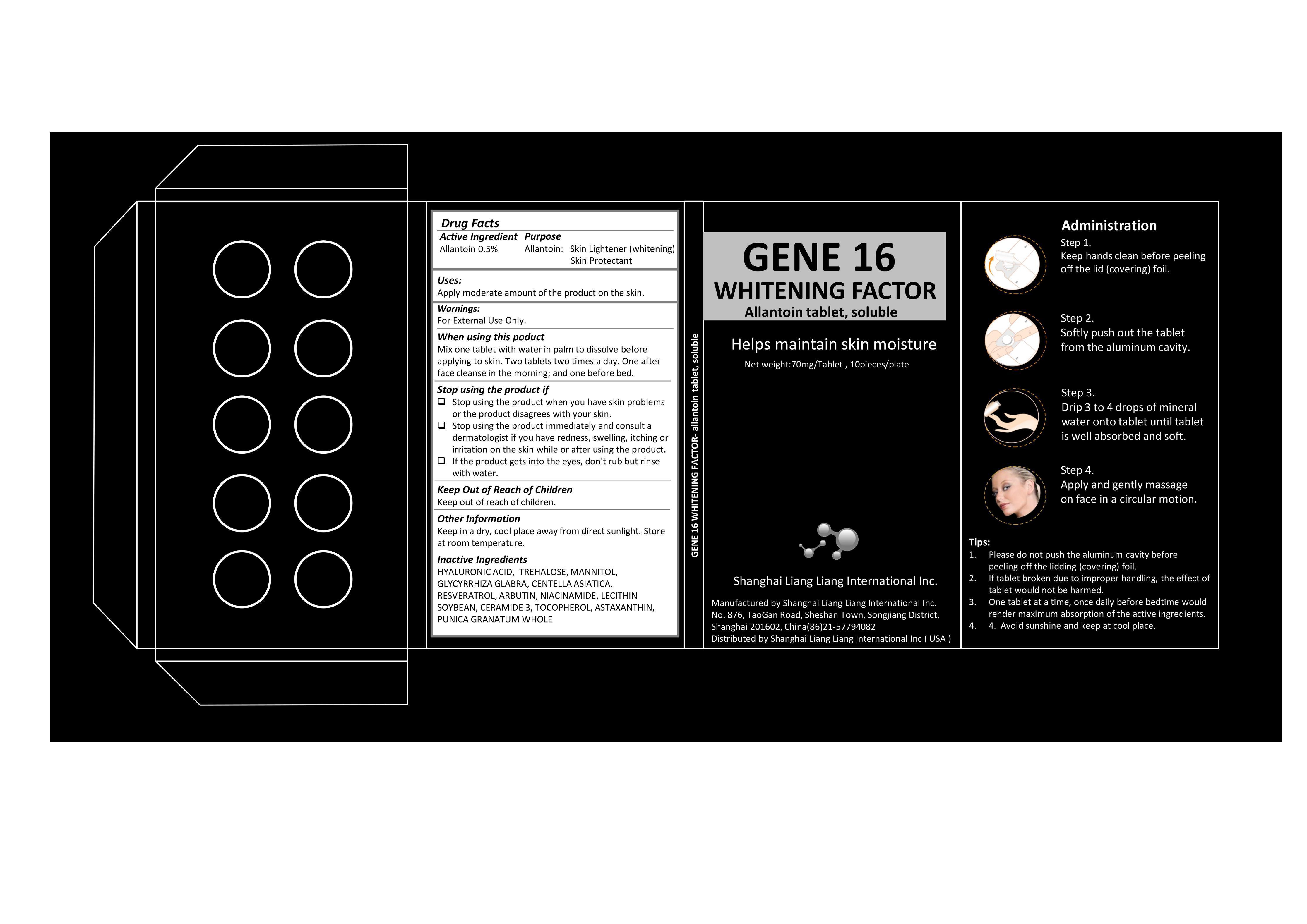 DRUG LABEL: Gene 16 Whitening Factor
NDC: 69764-001 | Form: TABLET, SOLUBLE
Manufacturer: Shanghai Liangliang Bio Technology Co., Ltd
Category: otc | Type: HUMAN OTC DRUG LABEL
Date: 20260123

ACTIVE INGREDIENTS: ALLANTOIN 0.5 mg/100 mg
INACTIVE INGREDIENTS: HYALURONIC ACID; TREHALOSE; MANNITOL; GLYCYRRHIZA GLABRA; CENTELLA ASIATICA; RESVERATROL; ARBUTIN; NIACINAMIDE; LECITHIN, SOYBEAN; CERAMIDE 3; TOCOPHEROL; ASTAXANTHIN; PUNICA GRANATUM WHOLE

Shanghai Liangliang Bio Technology Co., Ltd

Active Ingredient

Allantoin 0.5%

Purpose

Allantoin Skin Lightener

Skin Protectant

Warning

For External Use Only.

Use

Apply moderate amount of the product on the skin.

Stop Using the Product if

Stop using the product when you have skin problems or the product disagrees with your skin.
・Stop using the product immediately and consult a dermatologist if you have redness, swelling, itching or irritation on the skin while or after using the product.
・If the product gets into the eyes, don't rub but rinse with water.

Keep Out of Reach of Children

When Using the Product

Mix one tablet with water in palm to dissolve before applying to skin. Two tablets two times a day. One after face cleanse in the morning; and one before bed.

Other Information

Keep in a dry, cool place away from direct sunlight. Store at room temperature.

Contact the Manufacturer or Distributor

Manufactured by Shanghai Liangliang Bio Technology Co., Ltd
No. 876, TaoGan Road, Sheshan Town, Songjiang District, Shanghai 201602, China
(86)21-57794082

Distributed by Shanghai Liangliang Bio Technology Co., Ltd (USA)

Inactive Ingredients

HYALURONIC ACID, TREHALOSE, MANNITOL, GLYCYRRHIZA GLABRA, CENTELLA ASIATICA, RESVERATROL, ARBUTIN, NIACINAMIDE, LECITHIN SOYBEAN, CERAMIDE 3, TOCOPHEROL, ASTAXANTHIN, PUNICA GRANATUM WHOLE